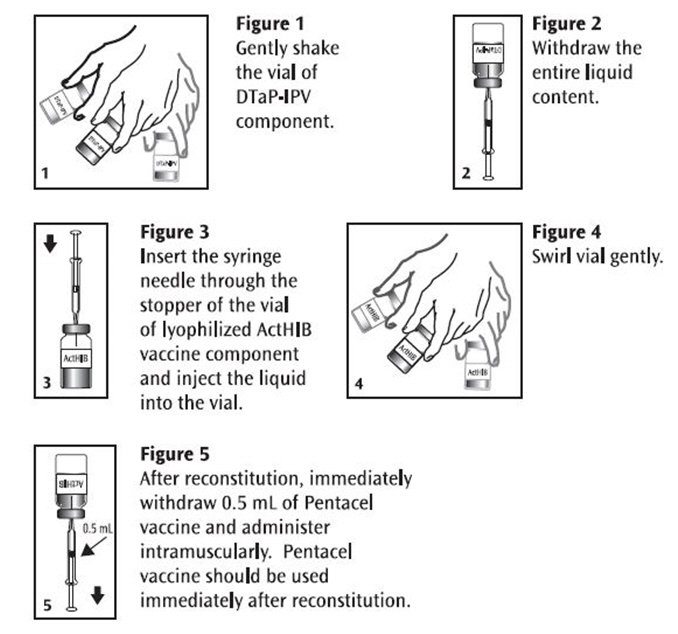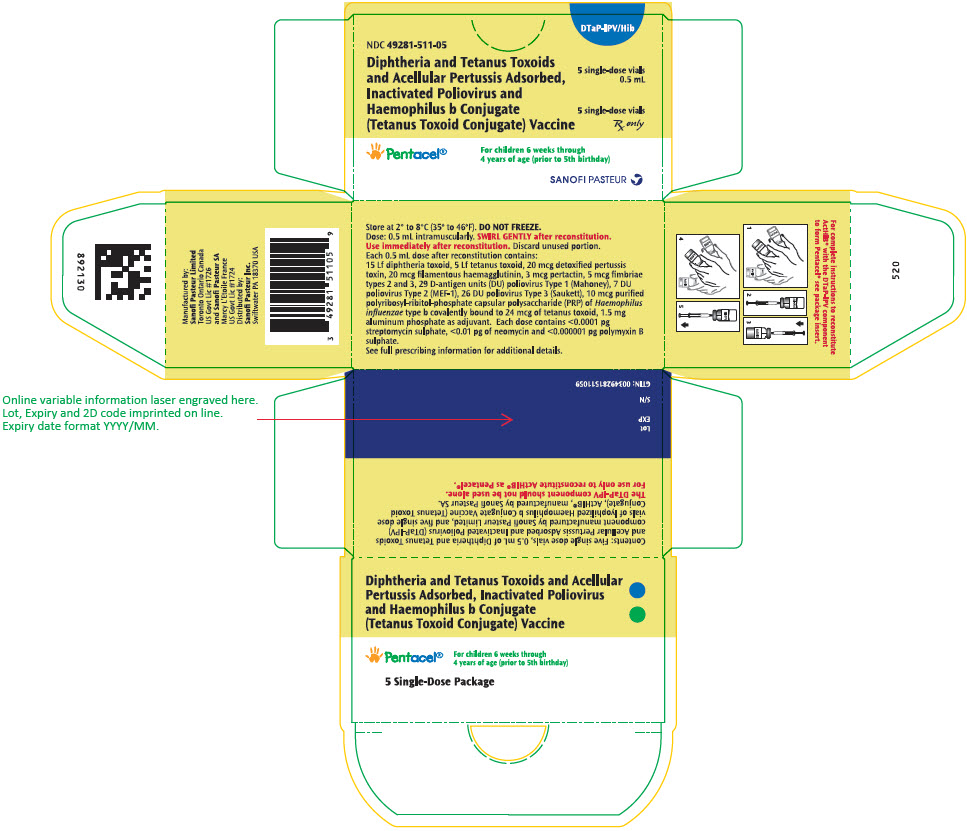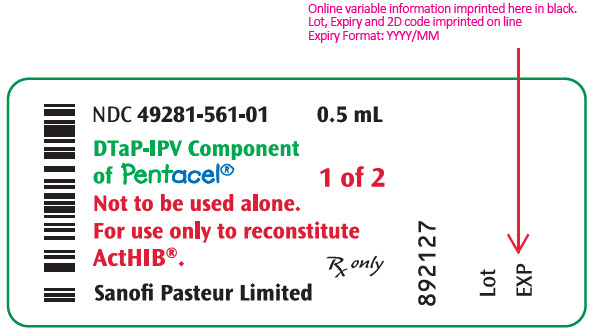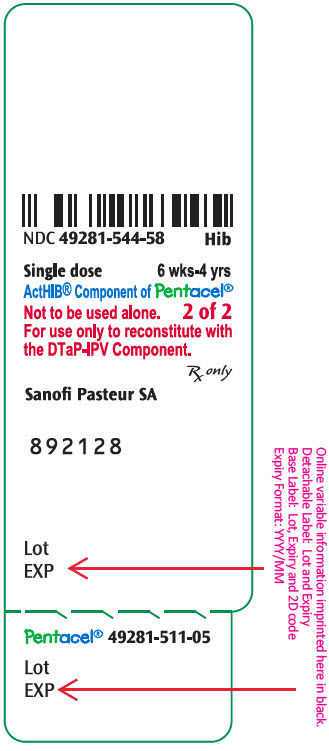 DRUG LABEL: PENTACEL
NDC: 49281-511 | Form: KIT | Route: INTRAMUSCULAR
Manufacturer: Sanofi Pasteur Inc.
Category: other | Type: VACCINE LABEL
Date: 20251113

ACTIVE INGREDIENTS: CORYNEBACTERIUM DIPHTHERIAE TOXOID ANTIGEN (FORMALDEHYDE INACTIVATED) 15 [Lf]/0.5 mL; CLOSTRIDIUM TETANI TOXOID ANTIGEN (FORMALDEHYDE INACTIVATED) 5 [Lf]/0.5 mL; BORDETELLA PERTUSSIS TOXOID ANTIGEN (GLUTARALDEHYDE INACTIVATED) 20 ug/0.5 mL; BORDETELLA PERTUSSIS FILAMENTOUS HEMAGGLUTININ ANTIGEN (FORMALDEHYDE INACTIVATED) 20 ug/0.5 mL; BORDETELLA PERTUSSIS PERTACTIN ANTIGEN 3 ug/0.5 mL; BORDETELLA PERTUSSIS FIMBRIAE 2/3 ANTIGEN 5 ug/0.5 mL; POLIOVIRUS TYPE 1 ANTIGEN (FORMALDEHYDE INACTIVATED) 29 [D'ag'U]/0.5 mL; POLIOVIRUS TYPE 2 ANTIGEN (FORMALDEHYDE INACTIVATED) 7 [D'ag'U]/0.5 mL; POLIOVIRUS TYPE 3 ANTIGEN (FORMALDEHYDE INACTIVATED) 26 [D'ag'U]/0.5 mL; HAEMOPHILUS INFLUENZAE TYPE B STRAIN 1482 CAPSULAR POLYSACCHARIDE TETANUS TOXOID CONJUGATE ANTIGEN 10 ug/0.5 mL
INACTIVE INGREDIENTS: ALUMINUM PHOSPHATE 1.5 mg/0.5 mL; PHENOXYETHANOL 3.3 mg/0.5 mL; POLYSORBATE 80; GLUTARAL; FORMALDEHYDE; ALBUMIN BOVINE; STREPTOMYCIN SULFATE; NEOMYCIN; POLYMYXIN B SULFATE; WATER; Sucrose 42.5 mg/0.5 mL

HIGHLIGHTS OF PRESCRIBING INFORMATION

These highlights do not include all the information needed to use Pentacel safely and effectively. See full prescribing information for Pentacel.
Pentacel (Diphtheria and Tetanus Toxoids and Acellular Pertussis Adsorbed, Inactivated Poliovirus and Haemophilus b Conjugate (Tetanus Toxoid Conjugate) Vaccine
Suspension for Intramuscular Injection
Initial U.S. Approval: 2008

1 INDICATIONS AND USAGE

- Pentacel is a vaccine indicated for active immunization against diphtheria, tetanus, pertussis, poliomyelitis and invasive disease due to Haemophilus influenzae type b. Pentacel is approved for use as a four dose series in children 6 weeks through 4 years of age (prior to 5th birthday). (1)

2 DOSAGE AND ADMINISTRATION

- The four dose immunization series consists of a 0.5 mL intramuscular injection, after reconstitution, administered at 2, 4, 6 and 15-18 months of age. (2.1)
- Pentacel consists of a liquid vaccine component (DTaP-IPV component) and a lyophilized vaccine component (ActHIB vaccine). Reconstitute the ActHIB vaccine component with the DTaP-IPV component immediately before administration. (2.2)

3 DOSAGE FORMS AND STRENGTHS

- Suspension for injection (0.5 mL dose) supplied as a liquid vaccine component that is combined through reconstitution with a lyophilized vaccine component, both in single-dose vials. (3)

4 CONTRAINDICATIONS

- Severe allergic reaction (eg, anaphylaxis) after a previous dose of Pentacel, any ingredient of Pentacel, or any other diphtheria toxoid, tetanus toxoid, pertussis-containing vaccine, inactivated poliovirus vaccine or H. influenzae type b vaccine. (4.1)
- Encephalopathy within 7 days of a previous pertussis-containing vaccine with no other identifiable cause. (4.2)
- Progressive neurologic disorder until a treatment regimen has been established and the condition has stabilized. (4.3)

5 WARNINGS AND PRECAUTIONS

- Carefully consider benefits and risks before administering Pentacel to persons with a history of:
  - fever ≥40.5°C (≥105°F), hypotonic-hyporesponsive episode (HHE) or persistent, inconsolable crying lasting ≥3 hours within 48 hours after a previous pertussis-containing vaccine. (5.2)
  - seizures within 3 days after a previous pertussis-containing vaccine. (5.2)
- If Guillain-Barré syndrome occurred within 6 weeks of receipt of a prior vaccine containing tetanus toxoid, the risk for Guillain-Barré syndrome may be increased following Pentacel. (5.3)
- For infants and children with a history of previous seizures, an antipyretic may be administered (in the dosage recommended in its prescribing information) at the time of vaccination with Pentacel and for the next 24 hours. (5.4)
- Apnea following intramuscular vaccination has been observed in some infants born prematurely. The decision about when to administer an intramuscular vaccine, including Pentacel, to an infant born prematurely should be based on consideration of the individual infant's medical status and the potential benefits and possible risks of vaccination. (5.7)

6 ADVERSE REACTIONS

- Rates of adverse reactions varied by dose number. Systemic reactions that occurred in >50% of participants following any dose included fussiness/irritability and inconsolable crying. Fever ≥38.0°C occurred in 6-16% of participants, depending on dose number. Injection site reactions that occurred in >30% of participants following any dose included tenderness and increase in arm circumference. (6.1)

To report SUSPECTED ADVERSE REACTIONS, contact Pharmacovigilance Department, Sanofi Pasteur Inc., Discovery Drive, Swiftwater, PA 18370 at 1-800-822-2463 (1-800-VACCINE) or VAERS at 1-800-822-7967 and http://vaers.hhs.gov.

7 DRUG INTERACTIONS

- Do not mix Pentacel or any of its components with any other vaccine or diluent. (7.1)
- Immunosuppressive therapies may reduce the immune response to Pentacel. (7.2)
- Urine antigen detection may not have definitive diagnostic value in suspected H. influenzae type b disease within one week following Pentacel. (7.3)

FULL PRESCRIBING INFORMATION

1 INDICATIONS AND USAGE

Pentacel® is a vaccine indicated for active immunization against diphtheria, tetanus, pertussis, poliomyelitis and invasive disease due to Haemophilus influenzae type b. Pentacel is approved for use as a four dose series in children 6 weeks through 4 years of age (prior to fifth birthday).

2 DOSAGE AND ADMINISTRATION

For intramuscular injection only.

2.1 Immunization Series

Pentacel is to be administered as a 4-dose series at 2, 4, 6 and 15-18 months of age. The first dose may be given as early as 6 weeks of age. Four doses of Pentacel constitute a primary immunization course against pertussis. Three doses of Pentacel constitute a primary immunization course against diphtheria, tetanus, H. influenzae type b invasive disease, and poliomyelitis; the fourth dose is a booster for diphtheria, tetanus, H. influenzae type b invasive disease, and poliomyelitis immunizations [see Clinical Studies (14.1, 14.2, 14.3, 14.4, 14.5)].

Mixed Sequences of Pentacel and other DTaP-containing Vaccines

Pentacel, DAPTACEL (Diphtheria and Tetanus Toxoids and Acellular Pertussis Vaccine Adsorbed), Quadracel (Diphtheria and Tetanus Toxoids and Acellular Pertussis Adsorbed and Inactivated Poliovirus Vaccine), and VAXELIS (Diphtheria and Tetanus Toxoids and Acellular Pertussis, Inactivated Poliovirus, Haemophilus b Conjugate and Hepatitis B Vaccine) contain the same pertussis antigens manufactured by the same process. The amount of each of the pertussis antigens is the same in Pentacel, Quadracel, and VAXELIS. Pentacel contains twice the amount of detoxified pertussis toxin (PT) and four times the amount of filamentous hemagglutinin (FHA) as DAPTACEL.

Pentacel may be used as the fourth dose in the 5-dose DTaP series in children who have received a 3-dose series of VAXELIS [See CLINICAL STUDIES (14)].

Pentacel may be used to complete the first 4 doses of the 5-dose DTaP series in infants and children who have received 1 or more doses of DAPTACEL and are also scheduled to receive the other antigens of Pentacel.

Children who have completed a 4-dose series with Pentacel should receive a fifth dose of DTaP vaccine using DAPTACEL or Quadracel at 4-6 years of age. (1) (2)

Data are not available on the safety and effectiveness of using mixed sequences of Pentacel and DTaP vaccine from different manufacturers.

Mixed Sequences of Pentacel and IPV Vaccine

Pentacel may be used in infants and children who have received 1 or more doses of another licensed IPV vaccine and are scheduled to receive the antigens of Pentacel. However, data are not available on the safety and immunogenicity of Pentacel in such infants and children.

The Advisory Committee on Immunization Practices (ACIP) recommends that the final dose in the 4-dose IPV series be administered at age ≥4 years. (3) When Pentacel is administered at ages 2, 4, 6, and 15-18 months, an additional booster dose of IPV vaccine should be administered at age 4-6 years, resulting in a 5-dose IPV series. (3)

Mixed Sequences of Pentacel and Haemophilus b Conjugate Vaccine

Pentacel may be used to complete the vaccination series in infants and children previously vaccinated with one or more doses of Haemophilus b Conjugate Vaccine (either separately administered or as part of another combination vaccine), who are also scheduled to receive the other antigens of Pentacel. However, data are not available on the safety and immunogenicity of Pentacel in such infants and children. If different brands of Haemophilus b Conjugate Vaccines are administered to complete the series, three primary immunizing doses are needed, followed by a booster dose.

2.2 Administration

The package contains a vial of the DTaP-IPV (Vial 1 of 2) component and a vial of lyophilized ActHIB (Vial 2 of 2) vaccine component.

Before use, thoroughly but gently shake the vial of DTaP-IPV component, withdraw the entire liquid content and inject into the vial of the lyophilized ActHIB vaccine component. Gently swirl the vial now containing Pentacel until a cloudy, uniform, white to off-white (yellow tinge) suspension results. Parenteral drug products should be inspected visually for particulate matter and discoloration prior to administration, whenever solution and container permit. If these conditions exist, Pentacel should not be administered.

Withdraw and administer a single 0.5 mL dose of Pentacel intramuscularly. Pentacel should be used immediately after reconstitution. Discard unused portion. Refer to Figures 1, 2, 3, 4 and 5.

Pentacel: Instructions for Reconstitution of ActHIB Vaccine Component with DTaP-IPV Component

In infants younger than 1 year, the anterolateral aspect of the thigh provides the largest muscle and is the preferred site of injection. In older children, the deltoid muscle is usually large enough for injection. The vaccine should not be injected into the gluteal area or areas where there may be a major nerve trunk.

Do not administer this product intravenously or subcutaneously.

Pentacel should not be mixed in the same syringe with other parenteral products.

3 DOSAGE FORMS AND STRENGTHS

Pentacel is a suspension for injection (0.5 mL dose) supplied as a liquid vaccine component that is combined through reconstitution with a lyophilized vaccine component, both in single-dose vials [see Dosage and Administration (2.2) and How Supplied/Storage and Handling (16)].

4 CONTRAINDICATIONS

4.1 Hypersensitivity

A severe allergic reaction (eg, anaphylaxis) after a previous dose of Pentacel or any other diphtheria toxoid, tetanus toxoid, or pertussis-containing vaccine, inactivated poliovirus vaccine or H. influenzae type b vaccine, or any ingredient of this vaccine is a contraindication to administration of Pentacel [see Description (11)].

4.2 Encephalopathy

Encephalopathy (eg, coma, decreased level of consciousness, prolonged seizures) within 7 days of a previous dose of a pertussis containing vaccine that is not attributable to another identifiable cause is a contraindication to administration of any pertussis-containing vaccine, including Pentacel.

4.3 Progressive Neurologic Disorder

Progressive neurologic disorder, including infantile spasms, uncontrolled epilepsy, or progressive encephalopathy is a contraindication to administration of any pertussis-containing vaccine including Pentacel. Pertussis vaccine should not be administered to individuals with such conditions until a treatment regimen has been established and the condition has stabilized.

5 WARNINGS AND PRECAUTIONS

5.1 Management of Acute Allergic Reactions

Epinephrine hydrochloride solution (1:1,000) and other appropriate agents and equipment must be available for immediate use in case an anaphylactic or acute hypersensitivity reaction occurs.

5.2 Adverse Reactions Following Prior Pertussis Vaccination

If any of the following events occur within the specified period after administration of a pertussis vaccine, the decision to administer Pentacel should be based on careful consideration of potential benefits and possible risks.

- Temperature of ≥40.5°C (≥105°F) within 48 hours, not attributable to another identifiable cause.
- Collapse or shock-like state (hypotonic-hyporesponsive episode (HHE)) within 48 hours.
- Persistent, inconsolable crying lasting ≥3 hours within 48 hours.
- Seizures with or without fever within 3 days.

5.3 Guillain-Barré Syndrome and Brachial Neuritis

A review by the Institute of Medicine (IOM) found evidence for a causal relation between tetanus toxoid and both brachial neuritis and Guillain-Barré syndrome. (4) If Guillain-Barré syndrome occurred within 6 weeks of receipt of a prior vaccine containing tetanus toxoid, the risk for Guillain-Barré syndrome may be increased following Pentacel.

5.4 Infants and Children with a History of Previous Seizures

For infants or children with a history of previous seizures, an appropriate antipyretic may be administered (in the dosage recommended in its prescribing information) at the time of vaccination with a vaccine containing acellular pertussis antigens (including Pentacel) and for the following 24 hours, to reduce the possibility of post-vaccination fever.

5.5 Limitations of Vaccine Effectiveness

Vaccination with Pentacel may not protect all individuals.

5.6 Altered Immunocompetence

If Pentacel is administered to immunocompromised persons, including persons receiving immunosuppressive therapy, the expected immune response may not be obtained [see Drug Interactions (7.2)].

5.7 Apnea in Premature Infants

Apnea following intramuscular vaccination has been observed in some infants born prematurely. The decision about when to administer an intramuscular vaccine, including Pentacel, to an infant born prematurely should be based on consideration of the individual infant's medical status and the potential benefits and possible risks of vaccination.

5.8 Syncope

Syncope (fainting) may occur in association with administration of injectable vaccines including Pentacel. Procedures should be in place to avoid injury from fainting.

6 ADVERSE REACTIONS

Rates of adverse reactions varied by dose number. The most frequent (>50% of participants) systemic reactions following any dose were fussiness/irritability and inconsolable crying. The most frequent (>30% of participants) injection site reactions following any dose were tenderness and increased circumference of the injected arm.

6.1 Clinical Trials Experience

Because clinical trials are conducted under widely varying conditions, adverse reaction rates observed in the clinical trials of a vaccine cannot be directly compared to rates in the clinical trials of another vaccine and may not reflect the rates observed in practice. The adverse reaction information from clinical trials does, however, provide a basis for identifying the adverse events that appear to be related to vaccine use and for approximating rates of those events.

The poliovirus component (poliovirus types 1, 2, and 3) of this formulation of Pentacel is grown in Vero cells [see Description (11)]. The clinical study data in this section were accrued with a Pentacel formulation in which the poliovirus component was grown in MRC-5 cells. The safety of Pentacel was evaluated in four clinical studies in which a total of 5,980 participants received at least one dose of Pentacel. In three of the studies, conducted in the US, a total of 4,198 participants were enrolled to receive four consecutive doses of Pentacel. In the fourth study, conducted in Canada, 1,782 participants previously vaccinated with three doses of Pentacel received a fourth dose. The vaccination schedules of Pentacel, Control vaccines, and concomitantly administered vaccines used in these studies are provided in Table 1.

Across the four studies, 50.8% of participants were female. Among participants in the three US studies, 64.5% were Caucasian, 9.2% were Black, 12.9% were Hispanic, 3.9% were Asian, and 9.5% were of other racial/ethnic groups. In the two controlled studies, the racial/ethnic distribution of participants who received Pentacel and Control vaccines was similar. In the Canadian fourth dose study, 86.0% of participants were Caucasian, 1.9% were Black, 0.8% were Hispanic, 4.3% were Asian, 2.0% were East Indian, 0.5% were Native Indian, and 4.5% were of other racial/ethnic groups.

Table 1: Clinical Safety Studies of Pentacel: Vaccination Schedules
Study | Pentacel | Control Vaccines | Concomitantly Administered Vaccines
494-01 | 2, 4, 6 and 15 months | HCPDT + POLIOVAX + ActHIB at 2, 4, 6, and 15 months | 7-valent pneumococcal conjugate vaccine [PCV7 manufactured by Wyeth Laboratories.] (PCV7) at 2, 4, and 6 months in a subset of participants [PCV7 was introduced after the study was initiated, and thus, administered concomitantly with Pentacel vaccine in a subset of participants.] Hepatitis B vaccine at 2 and 6 months [The first dose of hepatitis B vaccine (manufacturer not specified) was administered prior to study initiation, from birth to 21 days of age. Subsequent doses were with hepatitis B vaccine manufactured by Merck and Co.]
P3T06 | 2, 4, 6, and 15-16 months | DAPTACEL + IPOL + ActHIB at 2, 4, and 6 months; and DAPTACEL + ActHIB at 15-16 months | PCV7 at 2, 4, and 6 months Hepatitis B vaccine at 2 and 6 months
494-03 | 2, 4, 6, and 15-16 months | None | PCV7 at 2, 4, and 6 months in all participants; and at 15 months in a random subset of participants Hepatitis B vaccine at 2 and 6 months (if a dose was previously administered) or at 2, 4, and 6 months (if no previous dose) Measles, mumps, rubella vaccine [MMR and varicella vaccines were both manufactured by Merck and Co.] (MMR) and varicella vaccine at 12 or 15 months in random subsets of participants
5A9908 | 15-18 months [Study participants previously had received three doses of Pentacel vaccine by 8 months of age.] | None | None
HCPDT: non-US licensed DTaP vaccine that is identical to the DTaP component of Pentacel.
POLIOVAX: US licensed Poliovirus Vaccine Inactivated, Sanofi Pasteur Limited.
IPOL: US licensed Poliovirus Vaccine Inactivated, Sanofi Winthrop Industrie.

Solicited Adverse Reactions

The incidence and severity of selected solicited injection site and systemic adverse reactions that occurred within 3 days following each dose of Pentacel or Control vaccines in Study P3T06 is shown in Table 2. Information on these reactions was recorded daily by parents or guardians on diary cards. In Table 2, injection site reactions are reported for the Pentacel and DAPTACEL injection sites.

Table 2: Number (Percentage) of Children with Selected Solicited Adverse Reactions by Severity Occurring within 0-3 days of Pentacel or Control Vaccines in Study P3T06
Injection Site Reactions | Pentacel Dose 1 N=465-467% | Pentacel Dose 2 N = 451 % | Pentacel Dose 3 N = 438-440 % | Pentacel Dose 4 N = 387-396 % | DAPTACEL Dose 1 N = 1,400-1,404 % | DAPTACEL Dose 2 N = 1,358-1,359 % | DAPTACEL Dose 3 N = 1,311-1,312 % | DAPTACEL Dose 4 N = 376-380 %
Redness >5 mm | 7.1 | 8.4 | 8.7 | 17.3 | 6.2 | 7.1 | 9.6 | 16.4
Redness >25 mm | 2.8 | 1.8 | 1.8 | 9.2 | 1.0 | 0.6 | 1.9 | 7.9
Redness >50 mm | 0.6 | 0.2 | 0.0 | 2.3 | 0.4 | 0.1 | 0.0 | 2.4
Swelling >5 mm | 7.5 | 7.3 | 5.0 | 9.7 | 4.0 | 4.0 | 6.5 | 10.3
Swelling >25 mm | 3.0 | 2.0 | 1.6 | 3.8 | 1.6 | 0.7 | 1.1 | 4.0
Swelling >50 mm | 0.9 | 0.0 | 0.0 | 0.8 | 0.4 | 0.1 | 0.1 | 1.3
Tenderness [Any: Mild, Moderate or Severe; Mild: subject whimpers when site is touched; Moderate: subject cries when site is touched; Severe: subject cries when leg or arm is moved.] Any | 47.5 | 39.2 | 42.7 | 56.1 | 48.8 | 38.2 | 40.9 | 51.1
Tenderness Moderate or Severe | 19.6 | 10.6 | 11.6 | 16.7 | 20.7 | 12.2 | 12.3 | 15.8
Tenderness Severe | 5.4 | 1.6 | 1.4 | 3.3 | 4.1 | 2.3 | 1.7 | 2.4
Increase in Arm Circumference >5 mm | - | - | - | 33.6 | - | - | - | 30.6
Increase in Arm Circumference >20 mm | - | - | - | 4.7 | - | - | - | 6.9
Increase in Arm Circumference >40 mm | - | - | - | 0.5 | - | - | - | 0.8
Systemic Reactions | Pentacel Dose 1 N = 466-467 % | Pentacel Dose 2 N = 451-452 % | Pentacel Dose 3 N = 435-440 % | Pentacel Dose 4 N = 389-398 % | DAPTACEL + IPOL + ActHIB Dose 1 N = 1,390-1,406 % | DAPTACEL + IPOL + ActHIB Dose 2 N = 1,346-1,360 % | DAPTACEL + IPOL + ActHIB Dose 3 N = 1,301-1,312 % | DAPTACEL + ActHIB Dose 4 N = 379-381 %
Fever [Fever is based upon actual temperatures recorded with no adjustments to the measurement route.] [Following Doses 1-3 combined, the proportion of temperature measurements that were taken by axillary, rectal or other routes, or not recorded were 46.0%, 53.0%, 1.0%, and 0% respectively, for Pentacel vaccine and 44.8%, 54.0%, 1.0%, and 0.1%, respectively, for DAPTACEL + IPOL + ActHIB. Following Dose 4, the proportion of temperature measurements that were taken by axillary, rectal or other routes, or not recorded were 62.7%, 34.4%, 2.4% and 0.5%, respectively, for Pentacel vaccine, and 61.1%, 36.6%, 1.7% and 0.5%, respectively, for DAPTACEL + ActHIB.] ≥38.0°C | 5.8 | 10.9 | 16.3 | 13.4 | 9.3 | 16.1 | 15.8 | 8.7
Fever >38.5°C | 1.3 | 2.4 | 4.4 | 5.1 | 1.6 | 4.3 | 5.1 | 3.2
Fever >39.5°C | 0.4 | 0.0 | 0.7 | 0.3 | 0.1 | 0.4 | 0.3 | 0.8
Decreased Activity/Lethargy [Moderate: interferes with or limits usual daily activity; Severe: disabling, not interested in usual daily activity.] Any | 45.8 | 32.7 | 32.5 | 24.1 | 51.1 | 37.4 | 33.2 | 24.1
Decreased Activity/Lethargy Moderate or Severe | 22.9 | 12.4 | 12.7 | 9.8 | 24.3 | 15.8 | 12.7 | 9.2
Decreased Activity/Lethargy Severe | 2.1 | 0.7 | 0.2 | 2.5 | 1.2 | 1.4 | 0.6 | 0.3
Inconsolable Crying Any | 59.3 | 49.8 | 47.3 | 35.9 | 58.5 | 51.4 | 47.9 | 36.2
Inconsolable Crying ≥1 hour | 19.7 | 10.6 | 13.6 | 11.8 | 16.4 | 16.0 | 12.2 | 10.5
Inconsolable Crying >3 hours | 1.9 | 0.9 | 1.1 | 2.3 | 2.2 | 3.4 | 1.4 | 1.8
Fussiness/Irritability Any | 76.9 | 71.2 | 68.0 | 53.5 | 75.8 | 70.7 | 67.1 | 53.8
Fussiness/Irritability ≥1 hour | 34.5 | 27.0 | 26.4 | 23.6 | 33.3 | 30.5 | 26.2 | 19.4
Fussiness/Irritability >3 hours | 4.3 | 4.0 | 5.0 | 5.3 | 5.6 | 5.5 | 4.3 | 4.5

Hypotonic Hyporesponsive Episodes

In Study P3T06, the diary cards included questions pertaining to HHEs. In Studies 494-01, 494-03, and 5A9908, a question about the occurrence of fainting or change in mental status was asked during post-vaccination phone calls. Across these 4 studies, no HHEs, as defined in a report of a US Public Health Service workshop (5) were reported among participants who received Pentacel (N = 5,979), separately administered HCPDT + POLIOVAX + ActHIB (N = 1,032) or separately administered DAPTACEL + IPOL + ActHIB (N = 1,455). Hypotonia not fulfilling HHE criteria within 7 days following vaccination was reported in 4 participants after the administration of Pentacel (1 on the same day as the 1st dose; 3 on the same day as the 3rd dose) and in 1 participant after the administration of DAPTACEL + IPOL + ActHIB (4 days following the 1st dose).

Seizures

Across Studies 494-01, 494-03, 5A9908 and P3T06, a total of 8 participants experienced a seizure within 7 days following either Pentacel (4 participants; N = 4,197 for at least one of Doses 1-3; N = 5,033 for Dose 4), separately administered HCPDT + POLIOVAX + ActHIB (3 participants; N = 1,032 for at least one of Doses 1-3, N = 739 for Dose 4), separately administered DAPTACEL + IPOL + ActHIB (1 participant; N = 1,455 for at least one of Doses 1-3), or separately administered DAPTACEL + ActHIB (0 participants; N = 418 for Dose 4). Among the four participants who experienced a seizure within 7 days following Pentacel, one participant in Study 494-01 had an afebrile seizure 6 days after the first dose, one participant in Study 494-01 had a possible seizure the same day as the third dose, and two participants in Study 5A9908 had a febrile seizure 2 and 4 days, respectively, after the fourth dose. Among the four participants who experienced a seizure within 7 days following Control vaccines, one participant had an afebrile seizure the same day as the first dose of DAPTACEL + IPOL + ActHIB, one participant had an afebrile seizure the same day as the second dose of HCPDT + POLIOVAX + ActHIB, and two participants had a febrile seizure 6 and 7 days, respectively, after the fourth dose of HCPDT + POLIOVAX + ActHIB.

Serious Adverse Events

In Study P3T06, within 30 days following any of Doses 1-3 of Pentacel or Control vaccines, 19 of 484 (3.9%) participants who received Pentacel and 50 of 1,455 (3.4%) participants who received DAPTACEL + IPOL + ActHIB experienced a serious adverse event. Within 30 days following Dose 4 of Pentacel or Control vaccines, 5 of 431 (1.2%) participants who received Pentacel and 4 of 418 (1.0%) participants who received DAPTACEL + ActHIB experienced a serious adverse event. In Study 494-01, within 30 days following any of Doses 1-3 of Pentacel or Control vaccines, 23 of 2,506 (0.9%) participants who received Pentacel and 11 of 1,032 (1.1%) participants who received HCPDT + POLIOVAX + ActHIB experienced a serious adverse event. Within 30 days following Dose 4 of Pentacel or Control vaccines, 6 of 1,862 (0.3%) participants who received Pentacel and 2 of 739 (0.3%) participants who received HCPDT + POLIOVAX + ActHIB experienced a serious adverse event.

Across Studies 494-01, 494-03 and P3T06, within 30 days following any of Doses 1-3 of Pentacel or Control vaccines, overall, the most frequently reported serious adverse events were bronchiolitis, dehydration, pneumonia and gastroenteritis. Across Studies 494-01, 494-03, 5A9908 and P3T06, within 30 days following Dose 4 of Pentacel or Control vaccines, overall, the most frequently reported serious adverse events were dehydration, gastroenteritis, asthma, and pneumonia.

Across Studies 494-01, 494-03, 5A9908 and P3T06, two cases of encephalopathy were reported, both in participants who had received Pentacel (N = 5,979). One case occurred 30 days post-vaccination and was secondary to cardiac arrest following cardiac surgery. One infant who had onset of neurologic symptoms 8 days post-vaccination was subsequently found to have structural cerebral abnormalities and was diagnosed with congenital encephalopathy.

A total of 5 deaths occurred during Studies 494-01, 494-03, 5A9908 and P3T06: 4 in children who had received Pentacel (N = 5,979) and one in a participant who had received DAPTACEL + IPOL + ActHIB (N = 1,455). There were no deaths reported in children who received HCPDT + POLIOVAX + ActHIB (N = 1,032). Causes of death among children who received Pentacel were asphyxia due to suffocation, head trauma, sudden infant death syndrome, and neuroblastoma (8, 23, 52 and 256 days post-vaccination, respectively). One participant with ependymoma died secondary to aspiration 222 days following DAPTACEL + IPOL + ActHIB.

6.2 Postmarketing Experience

The following additional adverse events have been spontaneously reported during the post-marketing use of Pentacel worldwide, since 1997. Between 1997 and 2007, Pentacel was primarily used in Canada. Because these events are reported voluntarily from a population of uncertain size, it may not be possible to reliably estimate their frequency or establish a causal relationship to vaccine exposure.

The following adverse events were included based on one or more of the following factors: severity, frequency of reporting, or strength of evidence for a causal relationship to Pentacel.

- Cardiac disorders
  Cyanosis
- Gastrointestinal disorders
  Vomiting, diarrhea
- General disorders and administration site conditions
  Injection site reactions (including inflammation, mass, abscess and sterile abscess), extensive swelling of the injected limb (including swelling that involved adjacent joints), vaccination failure/therapeutic response decreased (invasive H. influenzae type b disease)
- Immune system disorders
  Anaphylaxis/anaphylactic reaction, hypersensitivity (such as rash and urticaria)
- Infections and infestations
  Meningitis, rhinitis, viral infection
- Metabolism and nutrition disorders
  Decreased appetite
- Nervous system disorders
  Somnolence, HHE, depressed level of consciousness
- Psychiatric disorders
  Screaming
- Respiratory, thoracic and mediastinal disorders
  Apnea, cough
- Skin and subcutaneous tissue disorders
  Erythema, skin discoloration
- Vascular disorders
  Pallor

7 DRUG INTERACTIONS

7.1 Concomitant Administration with Other Vaccines

In clinical trials, Pentacel was administered concomitantly with one or more of the following US licensed vaccines: hepatitis B vaccine, 7-valent pneumococcal conjugate vaccine, MMR and varicella vaccines [see Adverse Reactions (6) and Clinical Studies (14)]. When Pentacel is given at the same time as another injectable vaccine(s), the vaccine(s) should be administered with different syringes and at different injection sites.

7.2 Immunosuppressive Treatments

Immunosuppressive therapies, including irradiation, antimetabolites, alkylating agents, cytotoxic drugs and corticosteroids (used in greater than physiologic doses), may reduce the immune response to Pentacel [see Warnings and Precautions (5.6)].

7.3 Drug/Laboratory Test Interactions

Antigenuria has been detected in some instances following receipt of ActHIB. Urine antigen detection may not have definite diagnostic value in suspected H. influenzae type b disease within one week following receipt of Pentacel. (6)

8 USE IN SPECIFIC POPULATIONS

8.4 Pediatric Use

The safety and effectiveness of Pentacel was established in the age group 6 weeks through 18 months on the basis of clinical studies [see Clinical Trials Experience (6.1) and Clinical Studies (14)]. The safety and effectiveness of Pentacel in the age group 19 months through 4 years is supported by evidence in children 6 weeks through 18 months. The safety and effectiveness of Pentacel in infants less than 6 weeks of age and in children 5 to 16 years of age have not been established.

11 DESCRIPTION

Pentacel consists of a Diphtheria and Tetanus Toxoids and Acellular Pertussis Adsorbed and Inactivated Poliovirus (DTaP-IPV) component and an ActHIB® component combined through reconstitution for intramuscular injection. ActHIB (Haemophilus b Conjugate Vaccine [Tetanus Toxoid Conjugate]), consists of H. influenzae type b capsular polysaccharide (polyribosyl-ribitol-phosphate [PRP]) covalently bound to tetanus toxoid (PRP-T). The DTaP-IPV component is supplied as a sterile liquid used to reconstitute the lyophilized ActHIB component to form Pentacel. Pentacel is a uniform, cloudy, white to off-white (yellow tinge) suspension.

Each 0.5 mL dose contains 15 Lf diphtheria toxoid, 5 Lf tetanus toxoid, acellular pertussis antigens [20 mcg detoxified pertussis toxin (PT), 20 mcg filamentous hemagglutinin (FHA), 3 mcg pertactin (PRN), 5 mcg fimbriae types 2 and 3 (FIM)], inactivated polioviruses [29 D-antigen units (DU) Type 1 (Mahoney), 7 DU Type 2 (MEF-1), 26 DU Type 3 (Saukett)] and 10 mcg PRP of H. influenzae type b covalently bound to 24 mcg of tetanus toxoid (PRP-T).

Other ingredients per 0.5 mL dose include 1.5 mg aluminum phosphate (0.33 mg aluminum) as the adjuvant, <8.1 mcg polysorbate 80, 3.3 mg (0.6% v/v) 2-phenoxyethanol (not as a preservative), 42.5 mg sucrose, 2 mcg to 7 mcg residual formaldehyde, <50 ng residual glutaraldehyde, ≤10 ng residual bovine serum albumin, <0.0001 pg streptomycin sulphate, <0.01 pg of neomycin and <0.000001 pg polymyxin B sulphate.

Corynebacterium diphtheriae is grown in modified Mueller's growth medium. (7) After purification by ammonium sulfate fractionation, the diphtheria toxin is detoxified with formaldehyde and diafiltered.

Clostridium tetani is grown in modified Mueller-Miller casamino acid medium without beef heart infusion. (8) Tetanus toxin is detoxified with formaldehyde and purified by ammonium sulfate fractionation and diafiltration. Diphtheria and tetanus toxoids are individually adsorbed onto aluminum phosphate.

The acellular pertussis vaccine antigens are produced from Bordetella pertussis cultures grown in Stainer-Scholte medium (9) modified by the addition of casamino acids and dimethyl-beta-cyclodextrin. PT, FHA and PRN are isolated separately from the supernatant culture medium. FIM are extracted and copurified from the bacterial cells. The pertussis antigens are purified by sequential filtration, salt-precipitation, ultrafiltration and chromatography. PT is detoxified with glutaraldehyde. FHA is treated with formaldehyde and the residual aldehydes are removed by ultrafiltration. The individual antigens are adsorbed separately onto aluminum phosphate.

The Type 1, Type 2, and Type 3 polioviruses are individually grown in Vero cells (a continuous line of monkey kidney cells). Prior to viral propagation, the cells are grown in Iscove's medium, supplemented with calf serum. For viral propagation, the culture medium is replaced by M199 medium without calf serum. The viral harvests are concentrated and purified, then inactivated with formaldehyde to produce monovalent suspensions of each serotype. Specified quantities of monovalent suspensions of each serotype are mixed to produce the trivalent poliovirus concentrate.

The adsorbed diphtheria, tetanus and acellular pertussis antigens are combined with aluminum phosphate (as adjuvant), 2-phenoxyethanol (not as a preservative) and water for injection, into an intermediate concentrate. The trivalent poliovirus concentrate is added and the DTaP-IPV component is diluted to its final concentration. The DTaP-IPV component does not contain a preservative.

Both diphtheria and tetanus toxoids induce at least 2 neutralizing units per mL in the guinea pig potency test. The potency of the acellular pertussis antigens is evaluated by the antibody response of immunized mice to detoxified PT, FHA and FIM as measured by enzyme-linked immunosorbent assay (ELISA). The potency of the PRN component of acellular pertussis antigens is measured by in vitro PRN antigenicity ELISA. The potency of the inactivated poliovirus antigens is determined by using the in vitro D-Antigen ELISA for each serotype.

PRP, a high molecular weight polymer, is prepared from the Haemophilus influenzae type b strain 1482 grown in a semi-synthetic medium. (10) The tetanus toxoid for conjugation to PRP is prepared by ammonium sulfate purification, and formalin inactivation of the toxin from cultures of Clostridium tetani (Harvard strain) grown in a modified Mueller and Miller medium. (11) The toxoid is filter sterilized prior to the conjugation process. The ActHIB component does not contain a preservative. Potency of the ActHIB component is specified on each lot by limits on the content of PRP polysaccharide and protein per dose and the proportion of polysaccharide and protein that is characterized as high molecular weight conjugate.

The vial stoppers for the DTaP-IPV and ActHIB components of Pentacel are not made with natural rubber latex.

12 CLINICAL PHARMACOLOGY

12.1 Mechanism of Action

Diphtheria

Diphtheria is an acute toxin-mediated disease caused by toxigenic strains of C. diphtheriae. Protection against disease is due to the development of neutralizing antibodies to diphtheria toxin. A serum diphtheria antitoxin level of 0.01 IU/mL is the lowest level giving some degree of protection. Antitoxin levels of at least 0.1 IU/mL are generally regarded as protective. (12) Levels of 1.0 IU/mL have been associated with long-term protection. (13)

Tetanus

Tetanus is an acute disease caused by an extremely potent neurotoxin produced by C. tetani. Protection against disease is due to the development of neutralizing antibodies to tetanus toxin. A serum tetanus antitoxin level of at least 0.01 IU/mL, measured by neutralization assay is considered the minimum protective level. (12) (14) A tetanus antitoxoid level ≥0.1 IU/mL as measured by the ELISA used in clinical studies of Pentacel is considered protective.

Pertussis

Pertussis (whooping cough) is a respiratory disease caused by B. pertussis. This Gram-negative coccobacillus produces a variety of biologically active components, though their role in either the pathogenesis of, or immunity to, pertussis has not been clearly defined.

Poliomyelitis

Polioviruses, of which there are three serotypes (Types 1, 2, and 3) are enteroviruses. The presence of poliovirus type-specific neutralizing antibodies has been correlated with protection against poliomyelitis. (15)

Invasive Disease Due to H. influenzae Type b

H. influenzae type b can cause invasive disease such as meningitis and sepsis. Anti-PRP antibody has been shown to correlate with protection against invasive disease due to H. influenzae type b.

Based on data from passive antibody studies (16) and an efficacy study with H. influenzae type b polysaccharide vaccine in Finland, (17) a post-vaccination anti-PRP level of 0.15 mcg/mL has been accepted as a minimal protective level. Data from an efficacy study with H. influenzae type b polysaccharide vaccine in Finland indicate that a level >1.0 mcg/mL 3 weeks after vaccination predicts protection through a subsequent one-year period. (18) (19) These levels have been used to evaluate the effectiveness of Haemophilus b Conjugate Vaccines, including the ActHIB component of Pentacel.

13 NONCLINICAL TOXICOLOGY

13.1 Carcinogenesis, Mutagenesis, Impairment of Fertility

Pentacel has not been evaluated for carcinogenic or mutagenic potential or impairment of fertility.

14 CLINICAL STUDIES

The efficacy of Pentacel is based on the immunogenicity of the individual antigens compared to separately administered vaccines. The poliovirus component (poliovirus types 1, 2 and 3) of this formulation of Pentacel is grown in Vero cells [see Description (11)]. The clinical study data in this section were accrued with a Pentacel formulation in which the poliovirus component was grown in MRC-5 cells. The poliovirus component of the two Pentacel formulations are analytically comparable. Serological correlates of protection exist for diphtheria, tetanus, poliomyelitis, and invasive disease due to H. influenzae type b [see Clinical Pharmacology (12.1)]. The efficacy against pertussis, for which there is no well established serological correlate of protection, was based, in part, on a comparison of pertussis immune responses following Pentacel in US children to responses following DAPTACEL (Diphtheria and Tetanus Toxoids and Acellular Pertussis Vaccine Adsorbed (DTaP) manufactured by Sanofi Pasteur Limited) in an efficacy study conducted in Sweden (Sweden I Efficacy Trial). While Pentacel and DAPTACEL contain the same pertussis antigens, manufactured by the same process, Pentacel contains twice as much detoxified PT and four times as much FHA as DAPTACEL.

Immune responses to Pentacel were evaluated in four US studies: Studies 494-01, P3T06, 494-03, and M5A10. The vaccination schedules of Pentacel, Control vaccines, and concomitantly administered vaccines used in Studies 494-01, P3T06, and 494-03 are provided in Table 1 [see Clinical Trials Experience (6.1)]. In Study M5A10, participants were randomized to receive Pentacel or separately administered DAPTACEL, IPOL, and ActHIB at 2, 4, and 6 months of age. 7-valent pneumococcal conjugate (PCV7, Wyeth Pharmaceuticals Inc.) at 2, 4, and 6 months of age, and Hepatitis B vaccine (Merck and Co. or GlaxoSmithKline Biologicals) at 2 and 6 months of age, were administered concomitantly with Pentacel or Control vaccines. (20)

14.1 Diphtheria

The proportions of participants achieving diphtheria antitoxin seroprotective levels one month following three and four doses of Pentacel or DAPTACEL in Study P3T06 are provided in Table 3.

14.2 Tetanus

The proportions of participants achieving tetanus antitoxoid seroprotective levels one month following three and four doses of Pentacel or DAPTACEL in Study P3T06 are provided in Table 3.

Table 3: Study P3T06 Diphtheria Antitoxin and Tetanus Antitoxoid Responses One Month Following Dose 3 and Dose 4 of Pentacel or DAPTACEL + IPOL + ActHIB in US Children Vaccinated at 2, 4, 6, and 15-16 Months of Age
Post-Dose 3 | Pentacel N = 331-345 | DAPTACEL + IPOL+ ActHIB N = 1,037-1,099
Diphtheria Antitoxin % ≥0.01 IU/mL [Seroprotection rate following Pentacel vaccine is not inferior to DAPTACEL vaccine (upper limit of 90% CI of the difference DAPTACEL – Pentacel is <10%).] | 100.0% | 100.0%
Diphtheria Antitoxin % ≥0.10 IU/mL [Non-inferiority criteria were not pre-specified.] | 98.8% | 98.5%
Tetanus Antitoxoid % ≥0.10 IU/mL | 99.7% | 100.0%
Post-Dose 4 | N = 341-352 | N = 328-334
Diphtheria Antitoxin % ≥0.10 IU/mL | 100.0% | 100.0%
Diphtheria Antitoxin % ≥1.0 IU/mL | 96.5% | 95.7%
Tetanus Antitoxoid % ≥0.10 IU/mL | 100.0% | 100.0%
Tetanus Antitoxoid % ≥1.0 IU/mL [With the ELISA used in this study, a tetanus antitoxoid level of 1.0 IU/mL is 10 times the protective level.] | 92.9% | 99.4%
Per Protocol Immunogenicity population.

14.3 Pertussis

In a clinical pertussis vaccine efficacy study conducted in Sweden during 1992-1995 (Sweden I Efficacy Trial), 2,587 infants received DAPTACEL and 2,574 infants received a non-US licensed DT vaccine as placebo at 2, 4, and 6 months of age. (1) The mean length of follow-up was 2 years after the third dose of vaccine. The protective efficacy of DAPTACEL against pertussis after 3 doses of vaccine using the World Health Organization (WHO) case definition (≥21 consecutive days of paroxysmal cough with culture or serologic confirmation or epidemiologic link to a confirmed case) was 84.9% (95% confidence interval [CI] 80.1%, 88.6%). The protective efficacy of DAPTACEL against mild pertussis (≥1 day of cough with laboratory confirmation) was 77.9% (95% CI 72.6%, 82.2%). Protection against pertussis by DAPTACEL was sustained for the 2-year follow-up period.

Based on comparisons of the immune responses to DAPTACEL in US infants (Post-Dose 3) and Canadian children (Post-Dose 4) relative to infants who participated in the Sweden I Efficacy Trial, it was concluded that 4 doses of DAPTACEL were needed for primary immunization against pertussis in US children. (1)

In a serology bridging analysis, immune responses to FHA, PRN and FIM in a subset of infants who received three doses of DAPTACEL in the Sweden I Efficacy Trial were compared to the Post-Dose 3 and Post-Dose 4 responses in a subset of US children from Study 494-01 who received Pentacel (Table 4). Available stored sera from infants who received DAPTACEL in the Sweden I Efficacy Trial and sera from children who received PCV7 concomitantly with the first three doses of Pentacel in Study 494-01 (Table 1) were assayed in parallel. Data on levels of antibody to PT using an adequately specific assay were not available for this serology bridging analysis.

Geometric mean antibody concentrations (GMCs) and seroconversion rates for antibodies to FHA, PRN and FIM one month following Dose 3 of DAPTACEL in the subset of infants from the Sweden I Efficacy Trial and one month following Dose 3 and Dose 4 of Pentacel in a subset of infants from US Study 494-01 are presented in Table 4. Seroconversion was defined as 4-fold rise in antibody level (Post-Dose 3/Pre-Dose 1 or Post-Dose 4/Pre-Dose 1). For anti-FHA and anti-FIM, the non-inferiority criteria were met for seroconversion rates, and for anti-FHA, anti-PRN, and anti-FIM, the non-inferiority criteria were met for GMCs, following Dose 4 of Pentacel relative to Dose 3 of DAPTACEL. The non-inferiority criterion for anti-PRN seroconversion following Dose 4 of Pentacel relative to Dose 3 of DAPTACEL was not met [upper limit of 95% CI for difference in rate (DAPTACEL minus Pentacel) = 13.24%]. Whether the lower anti-PRN seroconversion rate following Dose 4 of Pentacel in US children relative to Dose 3 of DAPTACEL in Swedish infants correlates with diminished efficacy of Pentacel against pertussis is unknown.

Table 4: FHA, PRN and FIM Antibody Responses One Month Following Dose 3 of DAPTACEL in a Subset of Infants Vaccinated at 2, 4, and 6 Months of Age in the Sweden I Efficacy Trial and One Month Following Dose 3 and Dose 4 of Pentacel in a Subset of Infants Vaccinated at 2, 4, 6, and 15-16 Months of Age in US Study 494-01
 | Post-Dose 3 DAPTACEL Sweden I Efficacy Trial N = 80 | Post-Dose 3 Pentacel [Non-inferiority criteria were not pre-specified for the comparisons of immune responses to Pentacel vaccine Post-Dose 3 vs. DAPTACEL vaccine Post-Dose 3.] US Study 494-01 N = 730-995 | Post-Dose 4 Pentacel [Pre-specified non-inferiority analyses compared immune responses to Pentacel vaccine Post-Dose 4 vs. DAPTACEL vaccine Post-Dose 3.] US Study 494-01 N = 507-554
Anti-FHA % achieving 4-fold rise [Fold rise was calculated as Post-Dose 3/Pre-Dose 1 antibody level or Post-Dose 4/Pre-Dose 1 antibody level.] GMC (EU/mL) | 68.8 40.70 | 79.8 71.46 | 91.7 [Percent achieving 4-fold rise or GMC Post-Dose 4 Pentacel vaccine is not inferior to Post-Dose 3 DAPTACEL vaccine [upper limit of 95% CI for difference in rates (DAPTACEL minus Pentacel) <10% and upper limit of 90% CI for GMC ratio (DAPTACEL/Pentacel) <1.5].] 129.85
Anti-PRN % achieving 4-fold rise GMC (EU/mL) | 98.8 111.26 | 74.4 38.11 | 89.2 [Non-inferiority criterion is not met for percent achieving 4-fold rise in anti-PRN Post-Dose 4 Pentacel vaccine relative to Post-Dose 3 DAPTACEL vaccine [upper limit of 95% CI for difference in rates (DAPTACEL minus Pentacel) = 13.24%, exceeds the non-inferiority criterion of <10%].] 90.82
Anti-FIM % achieving 4-fold rise GMC (EU/mL) | 86.3 339.31 | 86.5 265.02 | 91.5 506.57
Analyzed sera were from subsets of the Per Protocol Immunogenicity populations in each study.
Data on anti-PT levels using an adequately specific assay were not available.

In a separate study, Study P3T06, US infants were randomized to receive either Pentacel or DAPTACEL + IPOL + ActHIB at 2, 4, 6, and 15-16 months of age (Table 1). The pertussis immune responses (GMCs and seroconversion rates) one month following the third and fourth doses were compared between the two groups (Table 5). Seroconversion was defined as a 4-fold rise in antibody level (Post-Dose 3/Pre-Dose 1 or Post-Dose 4/Pre-Dose 1). Data on anti-PT responses obtained from an adequately specific assay were available on only a non-random subset of study participants. The subset of study participants was representative of all study participants with regard to Pre-Dose 1, Post-Dose 3 and Post-Dose 4 GMCs of antibodies to FHA, PRN and FIM. For each of the pertussis antigens, non-inferiority criteria were met for seroconversion rates and GMCs following Dose 3 of Pentacel relative to Dose 3 of DAPTACEL. Following Dose 4 of Pentacel relative to Dose 4 of DAPTACEL, non-inferiority criteria were met for all comparisons except for anti-PRN GMCs [upper limit of 90% CI for ratio of GMCs (DAPTACEL/Pentacel) = 2.25]. Whether the lower anti-PRN GMC following Dose 4 of Pentacel relative to Dose 4 of DAPTACEL in US children correlates with diminished efficacy of Pentacel against pertussis is unknown.

Table 5: Pertussis Antibody Responses One Month Following Doses 3 and 4 of Pentacel or DAPTACEL + IPOL + ActHIB in US Infants Vaccinated at 2, 4, 6, and 15-16 Months of Age in Study P3T06
 | Post-Dose 3 Pentacel N = 143 | Post-Dose 3 DAPTACEL + IPOL + ActHIB N = 481-485 | Post-Dose 4 Pentacel N = 113 | Post-Dose 4 DAPTACEL + ActHIB N = 127-128
Anti-PT % achieving 4-fold rise [Fold rise was calculated as Post-Dose 3/Pre-Dose 1 antibody level or Post-Dose 4/Pre-Dose 1 antibody level.] | 95.8 [Percent achieving 4-fold rise or GMC Post-Dose 3 Pentacel vaccine not inferior to Post-Dose 3 DAPTACEL vaccine [upper limit of 95% CI for GMC ratio (DAPTACEL/Pentacel) <1.5 and upper limit of 95% CI for differences in rates (DAPTACEL minus Pentacel) <10%].] | 87.3 | 93.8 [Percent achieving 4-fold rise or GMC Post-Dose 4 Pentacel vaccine not inferior to Post-Dose 4 DAPTACEL vaccine [upper limit of 95% CI for GMC ratio (DAPTACEL/Pentacel) <1.5 and upper limit of 95% CI for differences in rates (DAPTACEL minus Pentacel) <10%].] | 91.3
Anti-PT GMC (EU/mL) | 102.62 | 61.88 | 107.89 | 100.29
 | Post-Dose 3 Pentacel N = 218-318 | Post-Dose 3 DAPTACEL + IPOL + ActHIB N = 714-1,016 | Post-Dose 4 Pentacel N = 230-367 | Post-Dose 4 DAPTACEL + ActHIB N = 237-347
Anti-FHA % achieving 4-fold rise | 81.9 [Percent achieving 4-fold rise or GMC Post-Dose 3 Pentacel vaccine not inferior to Post-Dose 3 DAPTACEL vaccine [upper limit of 90% CI for GMC ratio (DAPTACEL/Pentacel) <1.5 and upper limit of 90% CI for differences in rates (DAPTACEL minus Pentacel) <10%].] | 60.9 | 88.4 [Percent achieving 4-fold rise or GMC Post-Dose 4 Pentacel vaccine not inferior to Post-Dose 4 DAPTACEL vaccine [upper limit of 90% CI for GMC ratio (DAPTACEL/Pentacel) <1.5 and upper limit of 90% CI for differences in rates (DAPTACEL minus Pentacel) <10%].] | 79.3
Anti-FHA GMC (EU/mL) | 73.68 | 29.22 | 107.94 | 64.02
Anti-PRN % achieving 4-fold rise | 74.2 | 75.4 | 92.7 | 98.3
Anti-PRN GMC (EU/mL) | 36.05 | 43.25 | 93.59 [Non-inferiority criterion is not met for GMC Post-Dose 4 Pentacel vaccine relative to Post-Dose 4 DAPTACEL vaccine [upper limit of 90% CI for GMC ratio (DAPTACEL/Pentacel) = 2.25, which exceeds the non-inferiority criterion of <1.5].] | 186.07
Anti-FIM % achieving 4-fold rise | 91.7 | 86.3 | 93.5 | 91.6
Anti-FIM GMC (EU/mL) | 268.15 | 267.18 | 553.39 | 513.54
Per Protocol Immunogenicity population for anti-FHA, anti-PRN, and anti-FIM.
Non-random subset of per Protocol Immunogenicity population for anti-PT. See text for further information on the subset evaluated.

Study 006 was a study conducted in the US, where infants were randomized to receive 3 doses of VAXELIS at 2, 4, and 6 months of age and Pentacel at 15 months of age (N = 2,406), or control group vaccines (4 doses of Pentacel at 2, 4, 6, and 15 months of age + RECOMBIVAX HB [Hepatitis B Vaccine (Recombinant)] at 2 and 6 months of age; N = 402). All subjects received concomitant Prevnar 13 (Pneumococcal 13-valent Conjugate Vaccine [Diphtheria CRM197 Protein]) at 2, 4, 6, and 15 months of age.

Participants were evaluated for immune responses to pertussis antigens one month following the dose of Pentacel administered at 15 months of age. The non-inferiority criteria for antibody vaccine response rates and GMCs for all pertussis antigens were met following the fourth dose except for GMCs for PRN (lower bound of 2-sided 95% CI for GMC ratio [VAXELIS group/Control group vaccines] was 0.66, which was below the non-inferiority criterion >0.67). (20)

14.4 Poliomyelitis

In Study P3T06 (Table 1), in which infants were randomized to receive the first three doses of Pentacel or DAPTACEL + IPOL + ActHIB at 2, 4, and 6 months of age, one month following the third dose of study vaccines, ≥99.4% of participants in both groups (Pentacel: N = 338-350), (DAPTACEL + IPOL + ActHIB: N = 1,050-1,097) achieved neutralizing antibody levels of ≥1:8 for Poliovirus types 1, 2, and 3.

In Study 494-01 (Table 1), in which infants were randomized to receive Pentacel or HCPDT + POLIOVAX + ActHIB, GMTs (1/dil) of antibodies to Poliovirus types 1, 2, and 3 one month following Dose 4 of Pentacel (N = 851-857) were 2,304, 4,178, and 4,415, respectively, and one month following Dose 4 of POLIOVAX (N = 284-287) were 2,330, 2,840, and 3,300, respectively.

14.5 Invasive Disease due to H. Influenzae Type b

Anti-PRP seroprotection rates and GMCs one month following Dose 3 of Pentacel or separately administered ActHIB in studies 494-01, P3T06, and M5A10 are presented in Table 6. In Study 494-01, non-inferiority criteria were not met for the proportion of participants who achieved an anti-PRP level ≥1.0 mcg/mL and for anti-PRP GMCs following Pentacel compared with separately administered ActHIB. In each of Studies P3T06 and M5A10, the non-inferiority criterion was met for the proportion of participants who achieved an anti-PRP level ≥1.0 mcg/mL following Pentacel compared with separately administered ActHIB. In Study M5A10, the non-inferiority criterion was met for anti-PRP GMCs following Pentacel compared with separately administered ActHIB.

Table 6: Anti-PRP Seroprotection Rates and GMCs One Month Following Three Doses of Pentacel or Separate DTaP + IPV + ActHIB Administered at 2, 4, and 6 Months of Age in Studies 494-01, P3T06, and M5A10
 | Study 494-01 Pentacel N = 1,127 | Study 494-01 HCPDT + POLIOVAX + ActHIB N = 401
% achieving anti-PRP ≥0.15 mcg/mL | 95.4 [Percent achieving specified level following Pentacel vaccine not inferior to ActHIB vaccine [upper limit of 90% CI for difference in rates (ActHIB minus Pentacel) <10%].] | 98.3
% achieving anti-PRP ≥1.0 mcg/mL | 79.1 [Non-inferiority criterion not met for percent achieving anti-PRP ≥1.0 mcg/mL following Pentacel vaccine relative to ActHIB vaccine [upper limit of 90% CI for difference in rates (ActHIB minus Pentacel), 12.9%, exceeds the non-inferiority criterion <10%].] | 88.8
Anti-PRP GMC (mcg/mL) | 3.19 [Non-inferiority criterion not met for GMC following Pentacel vaccine relative to ActHIB vaccine [upper limit of 90% CI of GMC ratio (ActHIB/Pentacel), 2.26, exceeds the non-inferiority criterion <1.5].] | 6.23
 | Study P3T06 Pentacel N = 365 | Study P3T06 DAPTACEL + IPOL + ActHIB N = 1,128
% achieving anti-PRP ≥0.15 mcg/mL | 92.3 | 93.3
% achieving anti-PRP ≥1.0 mcg/mL | 72.1 | 70.8
Anti-PRP GMC (mcg/mL) | 2.31 [Non-inferiority criterion not pre-specified.] | 2.29
 | Study M5A10 Pentacel N = 826 | Study M5A10 DAPTACEL + IPOL + ActHIB N = 421
% achieving anti-PRP ≥0.15 mcg/mL | 93.8 [Percent achieving specified level following Pentacel vaccine not inferior to ActHIB vaccine [upper limit of 95% CI for difference in rates (ActHIB minus Pentacel) <10%].] | 90.3
% achieving anti-PRP ≥1.0 mcg/mL | 75.1 | 74.8
Anti-PRP GMC (mcg/mL) | 2.52 [GMC following Pentacel vaccine not inferior to ActHIB vaccine [upper limit of 90% CI of GMC ratio (ActHIB/Pentacel) <1.5].] | 2.38
Per Protocol Immunogenicity population for all studies.
IPV indicates Poliovirus Vaccine Inactivated.

In Study 494-01, at 15 months of age prior to receipt of Dose 4 of study vaccines, 68.6% of Pentacel recipients (N = 829) and 80.8% of separately administered ActHIB recipients (N = 276) had an anti-PRP level ≥0.15 mcg/mL. Following Dose 4 of study vaccines, 98.2% of Pentacel recipients (N = 874) and 99.0% of separately administered ActHIB recipients (N = 291) had an anti-PRP level ≥1.0 mcg/mL.

In Study P3T06, at 15 months of age prior to receipt of Dose 4 of study vaccines, 65.4% of Pentacel recipients (N = 335) and 60.7% of separately administered ActHIB recipients (N = 323) had an anti-PRP level ≥0.15 mcg/mL. Following Dose 4 of study vaccines, 97.8% of Pentacel recipients (N = 361) and 95.9% of separately administered ActHIB recipients (N = 340) had an anti-PRP level ≥1.0 mcg/mL.

14.6 Concomitantly Administered Vaccines

In Study P3T06, (Table 1) there was no evidence for reduced antibody responses to hepatitis B vaccine (percent of participants with anti-HBsAg ≥10 mIU/mL and GMCs) or PCV7 (percent of participants with antibody levels ≥0.15 mcg/mL and ≥0.5 mcg/mL and GMCs to each serotype) administered concomitantly with Pentacel (N = 321-325) relative to these vaccines administered concomitantly with DAPTACEL + IPOL + ActHIB (N = 998-1,029). The immune responses to hepatitis B vaccine and PCV7 were evaluated one month following the third dose.

In Study 494-03, (Table 1) there was no evidence for interference in the immune response to the fourth dose of PCV7 (percent of participants with antibody levels ≥0.15 mcg/mL and ≥0.5 mcg/mL and GMCs to each serotype) administered at 15 months of age concomitantly with Pentacel (N = 155) relative to this vaccine administered concomitantly with MMR and varicella vaccines (N = 158). There was no evidence for interference in the immune response to MMR and varicella vaccines (percent of participants with pre-specified seroresponse level) administered at 15 months of age concomitantly with Pentacel (N = 154) relative to these vaccines administered concomitantly with PCV7 (N = 144). The immune responses to MMR, varicella vaccine and the fourth dose of PCV7 were evaluated one month post-vaccination.

15 REFERENCES

1 DAPTACEL® [full prescribing information]. Toronto, ON: Sanofi Pasteur Limited.
2 Quadracel® [full prescribing information]. Toronto, ON: Sanofi Pasteur Limited.
3 CDC. Updated recommendations of the Advisory Committee on Immunization Practices (ACIP) regarding routine poliovirus vaccination. MMWR 2009;58:829-30.
4 Stratton KR, et al. editors. Adverse events associated with childhood vaccines; evidence bearing on causality. Washington D.C.: National Academy Press. 1994. p. 67-117.
5 Braun MM. Report of a US Public Health Service workshop on hypotonic-hyporesponsive episode (HHE) after pertussis immunization. Pediatrics 1998;102(5)1-5.
6 Rothstein EP, et al. Comparison of antigenuria after immunization with three Haemophilus influenzae type b conjugate vaccines. Pediatr Infect Dis J 1991;10:311-4.
7 Stainer DW. Production of diphtheria toxin. In: Manclark CR, editor. Proceedings of an informal consultation on the World Health Organization requirements for diphtheria, tetanus, pertussis and combined vaccines. United States Public Health Service, Bethesda, MD. DHHS 91-1174. 1991. p. 7-11.
8 Mueller JH, Miller PA. Variable factors influencing the production of tetanus toxin. J Bacteriol 1954;67(3):271-7.
9 Stainer DW, et al. A simple chemically defined medium for the production of phase 1 Bordetella pertussis. J Gen Microbiol 1971;63:211-20.
10 Chu CY, et al. Further studies on the immunogenicity of Haemophilus influenzae type b and pneumococcal type 6A polysaccharide-protein conjugates. Infect Immun 1983;40:245-56.
11 Mueller JH, et al. Production of diphtheria toxin of high potency (100 Lf) on a reproducible medium. J Immunol 1941;40:21-32.
12 Department of Health and Human Services, Food and Drug Administration. Biological products; bacterial vaccines and toxoids; implementation of efficacy review; proposed rule. Federal Register 1985;50(240):51002-117.
13 Vitek CR, Tiwari TS, Wharton M. Diphtheria toxoid. In: Plotkin SA, Orenstein WA, Offit PA, editors. Vaccines. 7th ed. Philadelphia, PA: W. B. Saunders; 2018:7:261-75.
14 Roper M, Wassilak SGF, et al. Tetanus toxoid. In: Plotkin SA, Orenstein WA, Offit PA, editors. Vaccines. 7th ed. Philadelphia, PA: W.B. Saunders; 2018:18:1052-79.
15 Sutter RW, et al. Defining surrogate serologic tests with respect to predicting protective vaccine efficacy: Poliovirus vaccination. In: Williams JC, et al. eds. Combined vaccines and simultaneous administration. Current issues and perspectives. New York, NY: The New York Academy of Sciences. 1995:289-99.
16 Robbins JB, et al. Quantitative measurement of "natural" and immunization-induced Haemophilus influenzae type b capsular polysaccharide antibodies. Pediatr Res 1973;7:103-10.
17 Peltola H, et al. Haemophilus influenzae type b capsular polysaccharide vaccine in children: a double-blind field study of 100,000 vaccinees 3 months to 5 years of age in Finland. Pediatrics 1977;60:730-7.
18 Kayhty H, et al. The protective level of serum antibodies to the capsular polysaccharide of Haemophilus influenzae type b. J Infect Dis 1983;147:1100.
19 Anderson P. The protective level of serum antibodies to the capsular polysaccharide of Haemophilus influenzae type b. J Infect Dis 1984;149:1034.
20 VAXELIS® [full prescribing information]. Toronto, ON: MSP Vaccine Company.

16 HOW SUPPLIED/STORAGE AND HANDLING

16.1 How Supplied

The vial stoppers for the DTaP-IPV and ActHIB vaccine components of Pentacel are not made with natural rubber latex.

5 Dose Package (NDC No. 49281-511-05) containing 5 vials of DTaP-IPV (Vial 1 of 2) component (NDC No. 49281-561-01) to be used to reconstitute 5 single-dose vials of lyophilized ActHIB (Vial 2 of 2) vaccine component (NDC No. 49281-544-58).

16.2 Storage and Handling

Pentacel should be stored at 2° to 8°C (35° to 46°F). Do not freeze. Product which has been exposed to freezing should not be used. Do not use after expiration date shown on the label.

17 PATIENT COUNSELING INFORMATION

Before administration of Pentacel, health-care personnel should inform the parent or guardian of the benefits and risks of the vaccine and the importance of completing the immunization series unless a contraindication to further immunization exists.

The health-care provider should inform the parent or guardian about the potential for adverse reactions that have been temporally associated with Pentacel or other vaccines containing similar ingredients. The health-care provider should provide the Vaccine Information Statements (VIS) which are required by the National Childhood Vaccine Injury Act of 1986 to be given with each immunization. The parent or guardian should be instructed to report adverse reactions to their health-care provider.

Manufactured by:
Sanofi Pasteur Limited
Toronto Ontario Canada

and Sanofi Winthrop Industrie
Marcy L'Etoile France

Distributed by:
Sanofi Pasteur Inc.
Swiftwater PA 18370 USA

Pentacel® is a registered trademark of Sanofi, its affiliates and subsidiaries.

R4-1125 USA

PRINCIPAL DISPLAY PANEL - Kit Package

DTaP-IPV/Hib

NDC 49281-511-05

Diphtheria and Tetanus Toxoids
and Acellular Pertussis Adsorbed,
Inactivated Poliovirus and
Haemophilus b Conjugate
(Tetanus Toxoid Conjugate) Vaccine

5 single-dose vials
0.5 mL

5 single-dose vials

Rx only

Pentacel®

For children 6 weeks through
4 years of age (prior to 5th birthday)

SANOFI PASTEUR

PRINCIPAL DISPLAY PANEL - 0.5 mL Vial Label - 561

NDC 49281-561-01
0.5 mL

DTaP-IPV Component
of Pentacel®

1 of 2

Not to be used alone.

For use only to reconstitute
ActHIB®.
Rx only

Sanofi Pasteur Limited

PRINCIPAL DISPLAY PANEL - 0.5 mL Vial Label - 544

NDC 49281-544-58

Hib

Single dose
6 wks-4 yrs
ActHIB® Component of Pentacel®
Not to be used alone.
2 of 2
For use only to reconstitute with
the DTaP-IPV Component.

Rx only

Sanofi Pasteur SA